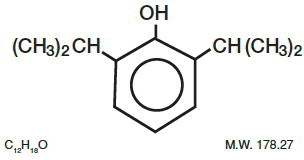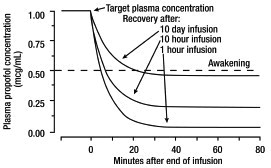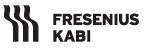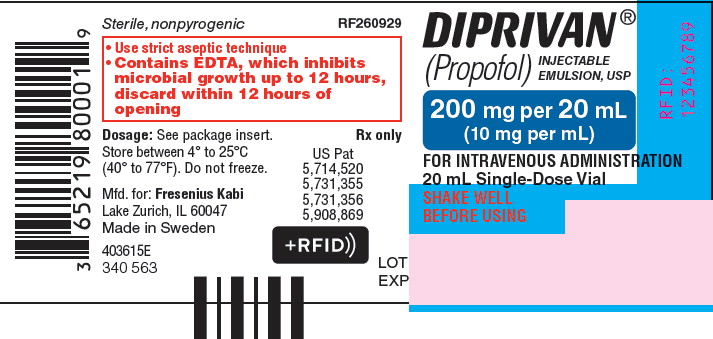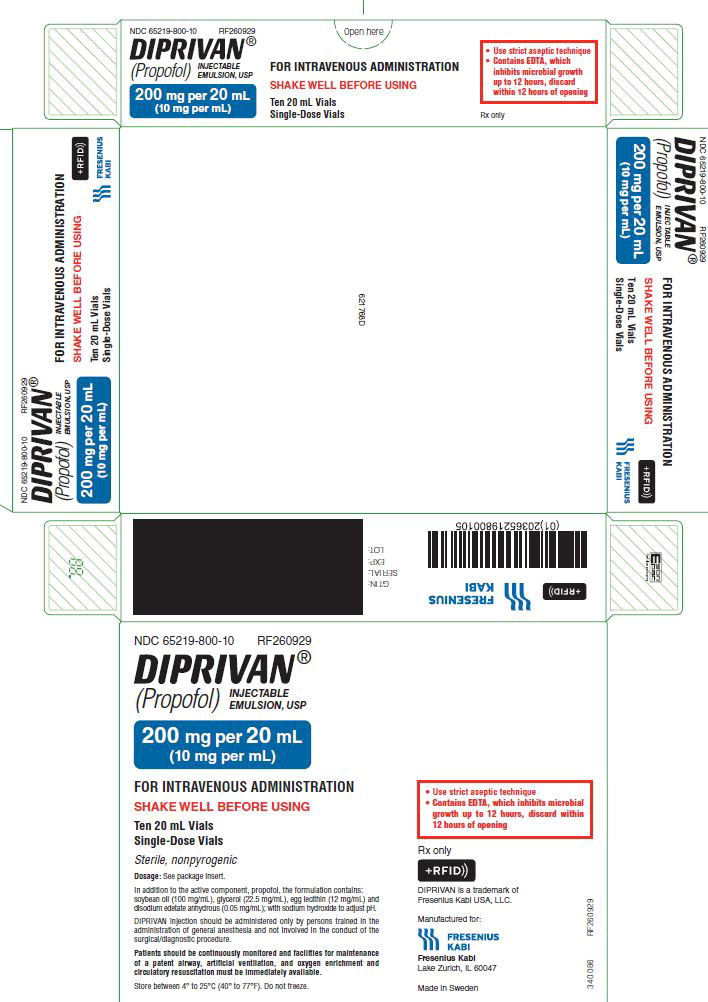 DRUG LABEL: Diprivan
NDC: 65219-800 | Form: INJECTION, EMULSION
Manufacturer: Fresenius Kabi USA, LLC
Category: prescription | Type: HUMAN PRESCRIPTION DRUG LABEL
Date: 20240418

ACTIVE INGREDIENTS: PROPOFOL 10 mg/1 mL
INACTIVE INGREDIENTS: SOYBEAN OIL 100 mg/1 mL; GLYCERIN 22.5 mg/1 mL; EGG PHOSPHOLIPIDS 12 mg/1 mL; EDETATE DISODIUM ANHYDROUS; SODIUM HYDROXIDE

Diprivan® (Propofol) Injectable Emulsion, USP

10 mg per mL

FOR INTRAVENOUS ADMINISTRATION
Strict aseptic technique must always be maintained during handling. DIPRIVAN is a single access parenteral product (single patient infusion vial) which contains 0.005% disodium edetate (EDTA) to inhibit the rate of growth of microorganisms, for up to 12 hours, in the event of accidental extrinsic contamination. However, DIPRIVAN can still support the growth of microorganisms, as it is not an antimicrobially preserved product under USP standards. Do not use if contamination is suspected. Discard unused drug product as directed within the required time limits. There have been reports in which failure to use aseptic technique when handling DIPRIVAN was associated with microbial contamination of the product and with fever, infection/sepsis, other life-threatening illness, and/or death.

There have been reports, in the literature and other public sources, of the transmission of bloodborne pathogens (such as Hepatitis B, Hepatitis C, and HIV) from unsafe injection practices, and use of propofol vials intended for single use on multiple persons. DIPRIVAN vials are never to be accessed more than once or used on more than one person.

(See WARNINGS and DOSAGE AND ADMINISTRATION, Handling Procedures).

DESCRIPTION:

DIPRIVAN® (propofol) injectable emulsion, USP is a sterile, nonpyrogenic emulsion containing 10 mg/mL of propofol suitable for intravenous administration. Propofol is chemically described as 2,6‑diisopropylphenol. The structural formula is:

Propofol is slightly soluble in water and, thus, is formulated in a white, oil-in-water emulsion. The pKa is 11. The octanol/water partition coefficient for propofol is 6761:1 at a pH of 6 to 8.5. In addition to the active component, propofol, the formulation also contains soybean oil (100 mg/mL), glycerol (22.5 mg/mL), egg lecithin (12 mg/mL); and disodium edetate anhydrous (0.05 mg/mL); with sodium hydroxide to adjust pH. DIPRIVAN is isotonic and has a pH of 7 to 8.5.

CLINICAL PHARMACOLOGY:

General

DIPRIVAN is an intravenous general anesthetic and sedation drug for use in the induction and maintenance of anesthesia or sedation. Intravenous injection of a therapeutic dose of propofol induces anesthesia, with minimal excitation, usually within 40 seconds from the start of injection (the time for one arm-brain circulation). As with other rapidly acting intravenous anesthetic agents, the half-time of the blood-brain equilibration is approximately 1 minute to 3 minutes, accounting for the rate of induction of anesthesia. The mechanism of action, like all general anesthetics, is poorly understood. However, propofol is thought to produce its sedative/anesthetic effects by the positive modulation of the inhibitory function of the neurotransmitter GABA through the ligand-gated GABAA receptors.

Pharmacodynamics

Pharmacodynamic properties of propofol are dependent upon the therapeutic blood propofol concentrations. Steady-state propofol blood concentrations are generally proportional to infusion rates. Undesirable side effects, such as cardiorespiratory depression, are likely to occur at higher blood concentrations which result from bolus dosing or rapid increases in infusion rates. An adequate interval (3 minutes to 5 minutes) must be allowed between dose adjustments in order to assess clinical effects.

The hemodynamic effects of DIPRIVAN during induction of anesthesia vary. If spontaneous ventilation is maintained, the major cardiovascular effect is arterial hypotension (sometimes greater than a 30% decrease) with little or no change in heart rate and no appreciable decrease in cardiac output. If ventilation is assisted or controlled (positive pressure ventilation), there is an increase in the incidence and the degree of depression of cardiac output. Addition of an opioid, used as a premedicant, further decreases cardiac output and respiratory drive.

If anesthesia is continued by infusion of DIPRIVAN, the stimulation of endotracheal intubation and surgery may return arterial pressure towards normal. However, cardiac output may remain depressed. Comparative clinical studies have shown that the hemodynamic effects of DIPRIVAN during induction of anesthesia are generally more pronounced than with other intravenous (IV) induction agents.

Induction of anesthesia with DIPRIVAN is frequently associated with apnea in both adults and pediatric patients. In adult patients who received DIPRIVAN (2 mg/kg to 2.5 mg/kg), apnea lasted less than 30 seconds in 7% of patients, 30 seconds to 60 seconds in 24% of patients, and more than 60 seconds in 12% of patients. In pediatric patients from birth through 16 years of age assessable for apnea who received bolus doses of DIPRIVAN (1 mg/kg to 3.6 mg/kg), apnea lasted less than 30 seconds in 12% of patients, 30 seconds to 60 seconds in 10% of patients, and more than 60 seconds in 5% of patients.

During maintenance of general anesthesia, DIPRIVAN causes a decrease in spontaneous minute ventilation usually associated with an increase in carbon dioxide tension which may be marked depending upon the rate of administration and concurrent use of other medications (e.g., opioids, sedatives, etc.).

During monitored anesthesia care (MAC) sedation, attention must be given to the cardiorespiratory effects of DIPRIVAN. Hypotension, oxyhemoglobin desaturation, apnea, and airway obstruction can occur, especially following a rapid bolus of DIPRIVAN. During initiation of MAC sedation, slow infusion or slow injection techniques are preferable over rapid bolus administration. During maintenance of MAC sedation, a variable rate infusion is preferable over intermittent bolus administration in order to minimize undesirable cardiorespiratory effects. In the elderly, debilitated, or American Society of Anesthesiologists Physical Status (ASA-PS) III or IV patients, rapid (single or repeated) bolus dose administration should not be used for MAC sedation (see WARNINGS).

Clinical and preclinical studies suggest that DIPRIVAN is rarely associated with elevation of plasma histamine levels.

Preliminary findings in patients with normal intraocular pressure indicate that DIPRIVAN produces a decrease in intraocular pressure which may be associated with a concomitant decrease in systemic vascular resistance.

Clinical studies indicate that DIPRIVAN when used in combination with hypocarbia increases cerebrovascular resistance and decreases cerebral blood flow, cerebral metabolic oxygen consumption, and intracranial pressure. DIPRIVAN does not affect cerebrovascular reactivity to changes in arterial carbon dioxide tension (see Clinical Trials, Neuroanesthesia).

Clinical studies indicate that DIPRIVAN does not suppress the adrenal response to ACTH.

Animal studies and limited experience in susceptible patients have not indicated any propensity of DIPRIVAN to induce malignant hyperthermia.

Hemosiderin deposits have been observed in the livers of dogs receiving DIPRIVAN containing 0.005% disodium edetate over a four-week period; the clinical significance of this is unknown.

Pharmacokinetics

The pharmacokinetics of propofol are well described by a three compartment linear model with compartments representing the plasma, rapidly equilibrating tissues, and slowly equilibrating tissues.

Following an IV bolus dose, there is rapid equilibration between the plasma and the brain, accounting for the rapid onset of anesthesia. Plasma levels initially decline rapidly as a result of both distribution and metabolic clearance. Distribution accounts for about half of this decline following a bolus of propofol. However, distribution is not constant over time, but decreases as body tissues equilibrate with plasma and become saturated. The rate at which equilibration occurs is a function of the rate and duration of the infusion. When equilibration occurs there is no longer a net transfer of propofol between tissues and plasma.

Discontinuation of the recommended doses of DIPRIVAN after the maintenance of anesthesia for approximately one hour, or for sedation in the ICU for one day, results in a prompt decrease in blood propofol concentrations and rapid awakening. Longer infusions (10 days of ICU sedation) result in accumulation of significant tissue stores of propofol, such that the reduction in circulating propofol is slowed and the time to awakening is increased.

By daily titration of DIPRIVAN dosage to achieve only the minimum effective therapeutic concentration, rapid awakening within 10 minutes to 15 minutes can occur even after long-term administration. If, however, higher than necessary infusion levels have been maintained for a long time, propofol redistribution from fat and muscle to the plasma can be significant and slow recovery.

The figure below illustrates the fall of plasma propofol levels following infusions of various durations to provide ICU sedation.

The large contribution of distribution (about 50%) to the fall of propofol plasma levels following brief infusions means that after very long infusions a reduction in the infusion rate is appropriate by as much as half the initial infusion rate in order to maintain a constant plasma level. Therefore, failure to reduce the infusion rate in patients receiving DIPRIVAN for extended periods may result in excessively high blood concentrations of the drug. Thus, titration to clinical response and daily evaluation of sedation levels are important during use of DIPRIVAN infusion for ICU sedation.

Adults

Propofol clearance ranges from 23 mL/kg/min to 50 mL/kg/min (1.6 L/min to 3.4 L/min in 70 kg adults). It is chiefly eliminated by hepatic conjugation to inactive metabolites which are excreted by the kidney. A glucuronide conjugate accounts for about 50% of the administered dose. Propofol has a steady-state volume of distribution (10-day infusion) approaching 60 L/kg in healthy adults. A difference in pharmacokinetics due to sex has not been observed. The terminal half-life of propofol after a 10-day infusion is 1 day to 3 days.

Geriatrics

With increasing patient age, the dose of propofol needed to achieve a defined anesthetic end point (dose-requirement) decreases. This does not appear to be an age-related change in pharmacodynamics or brain sensitivity, as measured by EEG burst suppression. With increasing patient age, pharmacokinetic changes are such that, for a given IV bolus dose, higher peak plasma concentrations occur, which can explain the decreased dose requirement. These higher peak plasma concentrations in the elderly can predispose patients to cardiorespiratory effects including hypotension, apnea, airway obstruction, and/or arterial oxygen desaturation. The higher plasma levels reflect an age-related decrease in volume of distribution and intercompartmental clearance. Lower doses are therefore recommended for initiation and maintenance of sedation and anesthesia in elderly patients (see DOSAGE AND ADMINISTRATION).

Pediatrics

The pharmacokinetics of propofol were studied in children between 3 years and 12 years of age who received DIPRIVAN for periods of approximately 1 hour to 2 hours. The observed distribution and clearance of propofol in these children were similar to adults.

Organ Failure

The pharmacokinetics of propofol do not appear to be different in people with chronic hepatic cirrhosis or chronic renal impairment compared to adults with normal hepatic and renal function. The effects of acute hepatic or renal failure on the pharmacokinetics of propofol have not been studied.

Clinical Trials

Anesthesia and Monitored Anesthesia Care (MAC) Sedation

Pediatric Anesthesia

DIPRIVAN was studied in clinical trials which included cardiac surgical patients. Most patients were 3 years of age or older. The majority of the patients were healthy ASA-PS I or II patients. The range of doses in these studies are described in Tables 1 and 2.

TABLE 1. PEDIATRIC INDUCTION OF ANESTHESIA

Age Range | Induction Dose Median (range) | Injection Duration Median (range)
Birth through 16 years | 2.5 mg/kg (1 mg/kg to 3.6 mg/kg) | 20 sec. (6 sec to 45 sec)

TABLE 2. PEDIATRIC MAINTENANCE OF ANESTHESIA

Age Range | Maintenance Dosage | Duration
2 months to 2 years | 199 mcg/kg/min (82 mcg/kg/min to 394 mcg/kg/min) | 65 minutes (12 minutes to 282 minutes)
2 to 12 years | 188 mcg/kg/min (12 mcg/kg/min to 1,041 mcg/kg/min) | 69 minutes (23 minutes to 374 minutes)
>12 through 16 years | 161 mcg/kg/min (84 mcg/kg/min to 359 mcg/kg/min) | 69 minutes (26 minutes to 251 minutes)

Neuroanesthesia

DIPRIVAN was studied in patients undergoing craniotomy for supratentorial tumors in two clinical trials. The mean lesion size (anterior/posterior x lateral) was 31 mm x 32 mm in one trial and 55 mm x 42 mm in the other trial respectively. Anesthesia was induced with a median DIPRIVAN dose of 1.4 mg/kg (range: 0.9 mg/kg to 6.9 mg/kg) and maintained with a median maintenance DIPRIVAN dose of 146 mcg/kg/min (range: 68 mcg/kg/min to 425 mcg/kg/min). The median duration of the DIPRIVAN maintenance infusion was 285 minutes (range: 48 minutes to 622 minutes).

DIPRIVAN was administered by infusion in a controlled clinical trial to evaluate its effect on cerebrospinal fluid pressure (CSFP). The mean arterial pressure was maintained relatively constant over 25 minutes with a change from baseline of -4% ± 17% (mean ± SD). The change in CSFP was -46% ± 14%. As CSFP is an indirect measure of intracranial pressure (ICP), DIPRIVAN, when given by infusion or slow bolus in combination with hypocarbia, is capable of decreasing ICP independent of changes in arterial pressure.

Intensive Care Unit (ICU) Sedation

Adult Patients

DIPRIVAN was compared to benzodiazepines and opioids in clinical trials involving ICU patients. Of these, 302 received DIPRIVAN and comprise the overall safety database for ICU sedation.

Across all clinical studies, the mean infusion maintenance rate for all DIPRIVAN patients was 27 ± 21 mcg/kg/min. The maintenance infusion rates required to maintain adequate sedation ranged from 2.8 mcg/kg/min to 130 mcg/kg/min. The infusion rate was lower in patients over 55 years of age (approximately 20 mcg/kg/min) compared to patients under 55 years of age (approximately 38 mcg/kg/min). Although there are reports of reduced analgesic requirements, most patients received opioids for analgesia during maintenance of ICU sedation. In these studies, morphine or fentanyl was used as needed for analgesia. Some patients also received benzodiazepines and/or neuromuscular blocking agents. During long-term maintenance of sedation, some ICU patients were awakened once or twice every 24 hours for assessment of neurologic or respiratory function.

In Medical and Postsurgical ICU studies comparing DIPRIVAN to benzodiazepine infusion or bolus, there were no apparent differences in maintenance of adequate sedation, mean arterial pressure, or laboratory findings. Like the comparators, DIPRIVAN reduced blood cortisol during sedation while maintaining responsivity to challenges with adrenocorticotropic hormone (ACTH). Case reports from the published literature generally reflect that DIPRIVAN has been used safely in patients with a history of porphyria or malignant hyperthermia.

In hemodynamically stable head trauma patients ranging in age from 19 years to 43 years, adequate sedation was maintained with DIPRIVAN or morphine. There were no apparent differences in adequacy of sedation, intracranial pressure, cerebral perfusion pressure, or neurologic recovery between the treatment groups. In literature reports of severely head-injured patients in Neurosurgical ICUs, DIPRIVAN infusion and hyperventilation, both with and without diuretics, controlled intracranial pressure while maintaining cerebral perfusion pressure. In some patients, bolus doses resulted in decreased blood pressure and compromised cerebral perfusion pressure.

DIPRIVAN was found to be effective in status epilepticus which was refractory to the standard anticonvulsant therapies. For these patients, as well as for ARDS/respiratory failure and tetanus patients, sedation maintenance dosages were generally higher than those for other critically ill patient populations.

Pediatric Patients

A single, randomized, controlled, clinical trial that evaluated the safety and effectiveness of DIPRIVAN versus standard sedative agents (SSA) was conducted on 327 pediatric ICU patients. Patients were randomized to receive either DIPRIVAN 2%, (113 patients), DIPRIVAN 1%, (109 patients), or an SSA (e.g., lorazepam, chloral hydrate, fentanyl, ketamine, morphine, or phenobarbital). DIPRIVAN therapy was initiated at an infusion rate of 5.5 mg/kg/hr and titrated as needed to maintain sedation at a standardized level. The results of the study showed an increase in the number of deaths in patients treated with DIPRIVAN as compared to SSAs. Of the 25 patients who died during the trial or within the 28-day follow-up period: 12 (11% were) in the DIPRIVAN 2% treatment group, 9 (8% were) in the DIPRIVAN 1% treatment group, and 4% were (4%) in the SSA treatment group. The differences in mortality rate between the groups were not statistically significant. Review of the deaths failed to reveal a correlation with underlying disease status or a correlation to the drug or a definitive pattern to the causes of death.

Cardiac Anesthesia

DIPRIVAN was evaluated in clinical trials involving patients undergoing coronary artery bypass graft (CABG).

In post-CABG (coronary artery bypass graft) patients, the maintenance rate of propofol administration was usually low (median 11 mcg/kg/min) due to the intraoperative administration of high opioid doses. Patients receiving DIPRIVAN required 35% less nitroprusside than midazolam patients. During initiation of sedation in post-CABG patients, a 15% to 20% decrease in blood pressure was seen in the first 60 minutes. It was not possible to determine cardiovascular effects in patients with severely compromised ventricular function.

INDICATIONS AND USAGE:

DIPRIVAN is an IV general anesthetic and sedation drug that can be used as described in the table below.

Table 3. Indications for DIPRIVAN

Indication | Approved Patient Population
Initiation and maintenance of Monitored Anesthesia Care (MAC) sedation | Adults only
Combined sedation and regional anesthesia | Adults only (see PRECAUTIONS)
Induction of General Anesthesia | Patients greater than or equal to 3 years of age
Maintenance of General Anesthesia | Patients greater than or equal to 2 months of age
Intensive Care Unit (ICU) sedation of intubated, mechanically ventilated patients | Adults only

Safety, effectiveness and dosing guidelines for DIPRIVAN have not been established for MAC Sedation in the pediatric population; therefore, it is not recommended for this use (see PRECAUTIONS, Pediatric Use).

DIPRIVAN is not recommended for induction of anesthesia below the age of 3 years or for maintenance of anesthesia below the age of 2 months because its safety and effectiveness have not been established in those populations.

In the Intensive Care Unit (ICU), DIPRIVAN can be administered to intubated, mechanically ventilated adult patients to provide continuous sedation and control of stress responses only by persons skilled in the medical management of critically ill patients and trained in cardiovascular resuscitation and airway management.

DIPRIVAN is not indicated for use in Pediatric ICU sedation since the safety of this regimen has not been established (see PRECAUTIONS, Pediatric Use).

DIPRIVAN is not recommended for obstetrics, including Cesarean section deliveries. DIPRIVAN crosses the placenta, and as with other general anesthetic agents, the administration of DIPRIVAN may be associated with neonatal depression (see PRECAUTIONS).

DIPRIVAN is not recommended for use in nursing mothers because propofol has been reported to be excreted in human milk, and the effects of oral absorption of small amounts of propofol are not known (see PRECAUTIONS).

CONTRAINDICATIONS:

DIPRIVAN is contraindicated in patients with a known hypersensitivity to propofol or any of DIPRIVAN components.

DIPRIVAN is contraindicated in patients with allergies to eggs, egg products, soybeans or soy products.

WARNINGS:

Use of DIPRIVAN has been associated with both fatal and life-threatening anaphylactic and anaphylactoid reactions.

For general anesthesia or monitored anesthesia care (MAC) sedation, DIPRIVAN should be administered only by persons trained in the administration of general anesthesia and not involved in the conduct of the surgical/diagnostic procedure. Sedated patients should be continuously monitored, and facilities for maintenance of a patent airway, providing artificial ventilation, administering supplemental oxygen, and instituting cardiovascular resuscitation must be immediately available. Patients should be continuously monitored for early signs of hypotension, apnea, airway obstruction, and/or oxygen desaturation. These cardiorespiratory effects are more likely to occur following rapid bolus administration, especially in the elderly, debilitated, or ASA-PS III or IV patients.

For sedation of intubated, mechanically ventilated patients in the Intensive Care Unit (ICU), DIPRIVAN should be administered only by persons skilled in the management of critically ill patients and trained in cardiovascular resuscitation and airway management.

Use of DIPRIVAN infusions for both adult and pediatric ICU sedation has been associated with a constellation of metabolic derangements and organ system failures, referred to as Propofol Infusion Syndrome, that have resulted in death. The syndrome is characterized by severe metabolic acidosis, hyperkalemia, lipemia, rhabdomyolysis, hepatomegaly, renal failure, ECG changes* and/or cardiac failure. The following appear to be major risk factors for the development of these events: decreased oxygen delivery to tissues; serious neurological injury and/or sepsis; high dosages of one or more of the following pharmacological agents: vasoconstrictors, steroids, inotropes and/or prolonged, high-dose infusions of propofol (greater than 5 mg/kg/h for greater than 48h). The syndrome has also been reported following large-dose, short-term infusions during surgical anesthesia. In the setting of prolonged need for sedation, increasing propofol dose requirements to maintain a constant level of sedation, or onset of metabolic acidosis during administration of a propofol infusion, consideration should be given to using alternative means of sedation.

*Coved ST segment elevation (similar to ECG changes of the Brugada syndrome).

Abrupt discontinuation of DIPRIVAN prior to weaning or for daily evaluation of sedation levels should be avoided. This may result in rapid awakening with associated anxiety, agitation, and resistance to mechanical ventilation. Infusions of DIPRIVAN should be adjusted to maintain a light level of sedation through the weaning process or evaluation of sedation level (see PRECAUTIONS).

DIPRIVAN should not be coadministered through the same IV catheter with blood or plasma because compatibility has not been established. In vitro tests have shown that aggregates of the globular component of the emulsion vehicle have occurred with blood/plasma/serum from humans and animals. The clinical significance of these findings is not known.

There have been reports in which failure to use aseptic technique when handling DIPRIVAN was associated with microbial contamination of the product and with fever, infection, sepsis, other life-threatening illness, and death. Do not use if contamination is suspected. Discard unused drug product as directed within the required time limits (see DOSAGE AND ADMINISTRATION, Handling Procedures).

There have been reports, in the literature and other public sources, of the transmission of bloodborne pathogens (such as Hepatitis B, Hepatitis C, and HIV) from unsafe injection practices, and use of propofol vials intended for single use on multiple persons. DIPRIVAN vial is never to be accessed more than once or used on more than one person.

Pediatric Neurotoxicity

Published animal studies demonstrate that the administration of anesthetic and sedation drugs that block NMDA receptors and/or potentiate GABA activity increase neuronal apoptosis in the developing brain and result in long-term cognitive deficits when used for longer than 3 hours. The clinical significance of these findings is not clear. However, based on the available data, the window of vulnerability to these changes is believed to correlate with exposures in the third trimester of gestation through the first several months of life, but may extend out to approximately three years of age in humans (see PRECAUTIONS, Pregnancy, Pediatric Use; ANIMAL TOXICOLOGY AND/OR PHARMACOLOGY).

Some published studies in children suggest that similar deficits may occur after repeated or prolonged exposures to anesthetic agents early in life and may result in adverse cognitive or behavioral effects. These studies have substantial limitations, and it is not clear if the observed effects are due to the anesthetic/sedation drug administration or other factors such as the surgery or underlying illness.

Anesthetic and sedation drugs are a necessary part of the care of children needing surgery, other procedures, or tests that cannot be delayed, and no specific medications have been shown to be safer than any other. Decisions regarding the timing of any elective procedures requiring anesthesia should take into consideration the benefits of the procedure weighed against the potential risks.

PRECAUTIONS:

General

Adult and Pediatric Patients

A lower induction dose and a slower maintenance rate of administration should be used in elderly, debilitated, or ASA-PS III or IV patients (see DOSAGE AND ADMINISTRATION). Patients should be continuously monitored for early signs of hypotension and/or bradycardia. Apnea requiring ventilatory support often occurs during induction and may persist for more than 60 seconds. DIPRIVAN use requires caution when administered to patients with disorders of lipid metabolism such as primary hyperlipoproteinemia, diabetic hyperlipemia, and pancreatitis.

Very rarely the use of DIPRIVAN may be associated with the development of a period of postoperative unconsciousness which may be accompanied by an increase in muscle tone. This may or may not be preceded by a brief period of wakefulness. Recovery is spontaneous.

When DIPRIVAN is administered to an epileptic patient, there is a risk of seizure during the recovery phase.

Attention should be paid to minimize pain on administration of DIPRIVAN. Transient local pain can be minimized if the larger veins of the forearm or antecubital fossa are used. Pain during intravenous injection may also be reduced by prior injection of IV lidocaine (1 mL of a 1% solution). Pain on injection occurred frequently in pediatric patients (45%) when a small vein of the hand was utilized without lidocaine pretreatment. With lidocaine pretreatment or when antecubital veins were utilized, pain was minimal (incidence less than 10%) and well-tolerated. There have been reports in the literature indicating that the addition of lidocaine to DIPRIVAN in quantities greater than 20 mg lidocaine/200 mg DIPRIVAN results in instability of the emulsion which is associated with increases in globule sizes over time and (in rat studies) a reduction in anesthetic potency. Therefore, it is recommended that lidocaine be administered prior to DIPRIVAN administration or that it be added to DIPRIVAN immediately before administration and in quantities not exceeding 20 mg lidocaine/200 mg DIPRIVAN.

Venous sequelae, i.e., phlebitis or thrombosis, have been reported rarely (less than 1%). In two clinical studies using dedicated intravenous catheters, no instances of venous sequelae were observed up to 14 days following induction.

Intra-arterial injection in animals did not induce local tissue effects. Accidental intra-arterial injection has been reported in patients, and, other than pain, there were no major sequelae.

Intentional injection into subcutaneous or perivascular tissues of animals caused minimal tissue reaction. During the post-marketing period, there have been rare reports of local pain, swelling, blisters, and/or tissue necrosis following accidental extravasation of DIPRIVAN.

Perioperative myoclonia, rarely including convulsions and opisthotonos, has occurred in association with DIPRIVAN administration.

Clinical features of anaphylaxis, including angioedema, bronchospasm, erythema, and hypotension, occur rarely following DIPRIVAN administration.

There have been rare reports of pulmonary edema in temporal relationship to the administration of DIPRIVAN, although a causal relationship is unknown.

Rarely, cases of unexplained postoperative pancreatitis (requiring hospital admission) have been reported after anesthesia in which DIPRIVAN was one of the induction agents used. Due to a variety of confounding factors in these cases, including concomitant medications, a causal relationship to DIPRIVAN is unclear.

DIPRIVAN has no vagolytic activity. Reports of bradycardia, asystole, and rarely, cardiac arrest have been associated with DIPRIVAN. Pediatric patients are susceptible to this effect, particularly when fentanyl is given concomitantly. The intravenous administration of anticholinergic agents (e.g., atropine or glycopyrrolate) should be considered to modify potential increases in vagal tone due to concomitant agents (e.g., succinylcholine) or surgical stimuli.

Intensive Care Unit Sedation

Adult Patients

(See WARNINGS and DOSAGE AND ADMINISTRATION, Handling Procedures.) The administration of DIPRIVAN should be initiated as a continuous infusion and changes in the rate of administration made slowly (greater than 5 min) in order to minimize hypotension and avoid acute overdosage (see DOSAGE AND ADMINISTRATION).

Patients should be monitored for early signs of significant hypotension and/or cardiovascular depression, which may be profound. These effects are responsive to discontinuation of DIPRIVAN, IV fluid administration, and/or vasopressor therapy. In the elderly, debilitated, or ASA-PS III or IV patients, rapid (single or repeated) bolus administration should not be used during sedation in order to minimize undesirable cardiorespiratory depression, including hypotension, apnea, airway obstruction, and oxygen desaturation.

As with other sedative medications, there is wide interpatient variability in DIPRIVAN dosage requirements, and these requirements may change with time.

Failure to reduce the infusion rate in patients receiving DIPRIVAN for extended periods may result in excessively high blood concentrations of the drug. Thus, titration to clinical response and daily evaluation of sedation levels are important during use of DIPRIVAN infusion for ICU sedation, especially when it is used for long durations.

Opioids and paralytic agents should be discontinued and respiratory function optimized prior to weaning patients from mechanical ventilation. Infusions of DIPRIVAN should be adjusted to maintain a light level of sedation prior to weaning patients from mechanical ventilatory support. Throughout the weaning process, this level of sedation may be maintained in the absence of respiratory depression. Because of the rapid clearance of DIPRIVAN, abrupt discontinuation of a patient's infusion may result in rapid awakening with associated anxiety, agitation, and resistance to mechanical ventilation, making weaning from mechanical ventilation difficult. It is therefore recommended that administration of DIPRIVAN be continued in order to maintain a light level of sedation throughout the weaning process until 10 minutes to 15 minutes prior to extubation, at which time the infusion can be discontinued.

Since DIPRIVAN is formulated in an oil-in-water emulsion, elevations in serum triglycerides may occur when DIPRIVAN is administered for extended periods of time. Patients at risk of hyperlipidemia should be monitored for increases in serum triglycerides or serum turbidity. Administration of DIPRIVAN should be adjusted if fat is being inadequately cleared from the body. A reduction in the quantity of concurrently administered lipids is indicated to compensate for the amount of lipid infused as part of the DIPRIVAN formulation; 1 mL of DIPRIVAN contains approximately 0.1 g of fat (1.1 kcal).

EDTA is a strong chelator of trace metals – including zinc. Although with DIPRIVAN there are no reports of decreased zinc levels or zinc deficiency-related adverse events, DIPRIVAN should not be infused for longer than 5 days without providing a drug holiday to safely replace estimated or measured urine zinc losses.

In clinical trials mean urinary zinc loss was approximately 2.5 mg/day to 3 mg/day in adult patients and 1.5 mg/day to 2 mg/day in pediatric patients.

In patients who are predisposed to zinc deficiency, such as those with burns, diarrhea, and/or major sepsis, the need for supplemental zinc should be considered during prolonged therapy with DIPRIVAN.

At high doses (2 grams to 3 grams per day), EDTA has been reported, on rare occasions, to be toxic to the renal tubules. Studies to date in patients with normal or impaired renal function have not shown any alteration in renal function with DIPRIVAN containing 0.005% disodium edetate. In patients at risk for renal impairment, urinalysis and urine sediment should be checked before initiation of sedation and then be monitored on alternate days during sedation.

The long-term administration of DIPRIVAN to patients with renal failure and/or hepatic insufficiency has not been evaluated.

Neurosurgical Anesthesia

When DIPRIVAN is used in patients with increased intracranial pressure or impaired cerebral circulation, significant decreases in mean arterial pressure should be avoided because of the resultant decreases in cerebral perfusion pressure. To avoid significant hypotension and decreases in cerebral perfusion pressure, an infusion or slow bolus of approximately 20 mg every 10 seconds should be utilized instead of rapid, more frequent, and/or larger boluses of DIPRIVAN. Slower induction, titrated to clinical responses, will generally result in reduced induction dosage requirements (1 mg/kg to 2 mg/kg). When increased ICP is suspected, hyperventilation and hypocarbia should accompany the administration of DIPRIVAN (see DOSAGE AND ADMINISTRATION).

Cardiac Anesthesia

Slower rates of administration should be utilized in premedicated patients, geriatric patients, patients with recent fluid shifts, and patients who are hemodynamically unstable. Fluid deficits should be corrected prior to administration of DIPRIVAN. In those patients where additional fluid therapy may be contraindicated, other measures, e.g., elevation of lower extremities, or use of pressor agents, may be useful to offset the hypotension which is associated with the induction of anesthesia with DIPRIVAN.

Information for Patients

Risk of Drowsiness

Patients should be advised that performance of activities requiring mental alertness, such as operating a motor vehicle, or hazardous machinery or signing legal documents may be impaired for some time after general anesthesia or sedation.

Effect of Anesthetic and Sedation Drugs on Early Brain Development

Studies conducted in young animals and children suggest repeated or prolonged use of general anesthetic or sedation drugs in children younger than 3 years may have negative effects on their developing brains. Discuss with parents and caregivers the benefits, risks, and timing and duration of surgery or procedures requiring anesthetic and sedation drugs (see WARNINGS, Pediatric Neurotoxicity).

Drug Interactions

The induction dose requirements of DIPRIVAN may be reduced in patients with intramuscular or intravenous premedication, particularly with narcotics (e.g., morphine, meperidine, and fentanyl, etc.) and combinations of opioids and sedatives (e.g., benzodiazepines, barbiturates, chloral hydrate, droperidol, etc.). These agents may increase the anesthetic or sedative effects of DIPRIVAN and may also result in more pronounced decreases in systolic, diastolic, and mean arterial pressures and cardiac output.

During maintenance of anesthesia or sedation, the rate of DIPRIVAN administration should be adjusted according to the desired level of anesthesia or sedation and may be reduced in the presence of supplemental analgesic agents (e.g., nitrous oxide or opioids). The concurrent administration of potent inhalational agents (e.g., isoflurane, enflurane, and halothane) during maintenance with DIPRIVAN has not been extensively evaluated. These inhalational agents can also be expected to increase the anesthetic or sedative and cardiorespiratory effects of DIPRIVAN.

The concomitant use of valproate and propofol may lead to increased blood levels of propofol. Reduce the dose of propofol when co-administering with valproate. Monitor patients closely for signs of increased sedation or cardiorespiratory depression.

DIPRIVAN does not cause a clinically significant change in onset, intensity or duration of action of the commonly used neuromuscular blocking agents (e.g., succinylcholine and nondepolarizing muscle relaxants).

No significant adverse interactions with commonly used premedications or drugs used during anesthesia or sedation (including a range of muscle relaxants, inhalational agents, analgesic agents, and local anesthetic agents) have been observed in adults. In pediatric patients, administration of fentanyl concomitantly with DIPRIVAN may result in serious bradycardia.

Carcinogenesis, Mutagenesis, Impairment of Fertility

Carcinogenesis

Long-term studies in animals have not been performed to evaluate the carcinogenic potential of propofol.

Mutagenesis

Propofol was not mutagenic in the in vitro bacterial reverse mutation assay (Ames test) using Salmonella typhimurium strains TA98, TA100, TA1535, TA1537 and TA1538. Propofol was not mutagenic in either the gene mutation/gene conversion test using Saccharomyces cerevisiae, or in vitro cytogenetic studies in Chinese hamsters. In the in vivo mouse micronucleus assay with Chinese hamsters propofol administration did not produce chromosome aberrations.

Impairment of Fertility

Female Wistar rats administered either 0, 10, or 15 mg/kg/day propofol intravenously from 2 weeks before pregnancy to day 7 of gestation did not show impaired fertility (0.65 and 1 times the human induction dose of 2.5 mg/kg based on body surface area). Male fertility in rats was not affected in a dominant lethal study at intravenous doses up to 15 mg/kg/day for 5 days.

Pregnancy

Risk Summary
There are no adequate and well-controlled studies in pregnant women. In animal reproduction studies, decreased pup survival concurrent with increased maternal mortality was observed with intravenous administration of propofol to pregnant rats either prior to mating and during early gestation or during late gestation and early lactation at exposures less than the human induction dose of 2.5 mg/kg. In pregnant rats administered 15 mg/kg/day intravenous propofol (equivalent to the human induction dose) from two weeks prior to mating to early in gestation (Gestation Day 7), offspring that were allowed to mate had increased postimplantation losses. The pharmacological activity (anesthesia) of the drug on the mother is probably responsible for the adverse effects seen in the offspring.

Published studies in pregnant primates demonstrate that the administration of anesthetic and sedation drugs that block NMDA receptors and/or potentiate GABA activity during the period of peak brain development increases neuronal apoptosis in the developing brain of the offspring when used for longer than 3 hours. There are no data on pregnancy exposures in primates corresponding to periods prior to the third trimester in humans [See Data].

The estimated background risk of major birth defects and miscarriage for the indicated population is unknown. All pregnancies have a background risk of birth defect, loss, or other adverse outcomes. In the U.S. general population, the estimated background risk of major birth defects and miscarriage in clinically recognized pregnancies is 2-4% and 15-20%, respectively.

Data

Animal Data

Pregnant rats were administered propofol intravenously at 0, 5, 10, and 15 mg/kg/day (0.3, 0.65, and 1 times the human induction dose of 2.5 mg/kg based on body surface area) during organogenesis (Gestational Days 6-15). Propofol did not cause adverse effects to the fetus at exposures up to 1 times the human induction dose despite evidence of maternal toxicity (decreased weight gain in all groups).

Pregnant rabbits were administered propofol intravenously at 0, 5, 10, and 15 mg/kg/day (0.65, 1.3, 2 times the human induction dose of 2.5 mg/kg based on body surface area comparison) during organogenesis (Gestation Days 6-18). Propofol treatment decreased total numbers of corpora lutea in all treatment groups but did not cause fetal malformations at any dose despite maternal toxicity (one maternal death from anesthesia-related respiratory depression in the high dose group).

Pregnant rats were administered propofol intravenously at 0, 10, and 15 mg/kg/day (0.65 and 1 times the human induction dose of 2.5 mg/kg based on body surface area) from late gestation through lactation (Gestation Day 16 to Lactation Day 22). Decreased pup survival was noted at all doses in the presence of maternal toxicity (deaths from anesthesia-induced respiratory depression). This study did not evaluate neurobehavioral function including learning and memory in the pups.

Pregnant rats were administered propofol intravenously at 0, 10, or 15 mg/kg/day (0.3 and 1 times the human induction dose of 2.5 mg/kg based on body surface area) from 2 weeks prior to mating to Gestational Day 7. Pup (F1) survival was decreased on Day 15 and 22 of lactation at maternally toxic doses of 10 and 15 mg/kg/day. When F1 offspring were allowed to mate, postimplantation losses were increased in the 15 mg/kg/day treatment group.

In a published study in primates, administration of an anesthetic dose of ketamine for 24 hours on Gestation Day 122 increased neuronal apoptosis in the developing brain of the fetus. In other published studies, administration of either isoflurane or propofol for 5 hours on Gestation Day 120 resulted in increased neuronal and oligodendrocyte apoptosis in the developing brain of the offspring. With respect to brain development, this time period corresponds to the third trimester of gestation in the human. The clinical significance of these findings is not clear; however, studies in juvenile animals suggest neuroapoptosis correlates with long-term cognitive deficits (see WARNINGS; Pediatric Neurotoxicity, PRECAUTIONS; Pediatric Use, and ANIMAL TOXICOLOGY AND/OR PHARMACOLOGY).

Labor and Delivery

DIPRIVAN is not recommended for obstetrics, including cesarean section deliveries. DIPRIVAN crosses the placenta, and as with other general anesthetic agents, the administration of DIPRIVAN may be associated with neonatal depression.

Nursing Mothers

DIPRIVAN is not recommended for use in nursing mothers because DIPRIVAN has been reported to be excreted in human milk and the effects of oral absorption of small amounts of propofol are not known.

Pediatric Use

The safety and effectiveness of DIPRIVAN have been established for induction of anesthesia in pediatric patients aged 3 years and older and for the maintenance of anesthesia aged 2 months and older.

DIPRIVAN is not recommended for the induction of anesthesia in patients younger than 3 years of age and for the maintenance of anesthesia in patients younger than 2 months of age as safety and effectiveness have not been established.

In pediatric patients, administration of fentanyl concomitantly with DIPRIVAN may result in serious bradycardia (see PRECAUTIONS, General).

DIPRIVAN is not indicated for use in pediatric patients for ICU sedation or for MAC sedation for surgical, nonsurgical or diagnostic procedures as safety and effectiveness have not been established.

There have been anecdotal reports of serious adverse events and death in pediatric patients with upper respiratory tract infections receiving DIPRIVAN for ICU sedation.

In one multicenter clinical trial of ICU sedation in critically ill pediatric patients that excluded patients with upper respiratory tract infections, the incidence of mortality observed in patients who received DIPRIVAN (n=222) was 9%, while that for patients who received standard sedative agents (n=105) was 4%. While causality has not been established, DIPRIVAN is not indicated for sedation in pediatric patients until further studies have been performed to document its safety in that population (see CLINICAL PHARMACOLOGY, Pharmacokinetics, Pediatric Patients and DOSAGE AND ADMINISTRATION).

In pediatric patients, abrupt discontinuation of DIPRIVAN following prolonged infusion may result in flushing of the hands and feet, agitation, tremulousness and hyperirritability. Increased incidences of bradycardia (5%), agitation (4%), and jitteriness (9%) have also been observed.

Published juvenile animal studies demonstrate that the administration of anesthetic and sedation drugs, such as DIPRIVAN, that either block NMDA receptors or potentiate the activity of GABA during the period of rapid brain growth or synaptogenesis, results in widespread neuronal and oligodendrocyte cell loss in the developing brain and alterations in synaptic morphology and neurogenesis. Based on comparisons across species, the window of vulnerability to these changes is believed to correlate with exposures in the third trimester of gestation through the first several months of life, but may extend out to approximately 3 years of age in humans.

In primates, exposure to 3 hours of ketamine that produced a light surgical plane of anesthesia did not increase neuronal cell loss, however, treatment regimens of 5 hours or longer of isoflurane increased neuronal cell loss. Data from isoflurane-treated rodents and ketamine-treated primates suggest that the neuronal and oligodendrocyte cell losses are associated with prolonged cognitive deficits in learning and memory. The clinical significance of these nonclinical findings is not known, and healthcare providers should balance the benefits of appropriate anesthesia in pregnant women, neonates, and young children who require procedures with the potential risks suggested by the nonclinical data (see WARNINGS, Pediatric Neurotoxicity, Pregnancy, ANIMAL TOXICOLOGY AND/OR PHARMACOLOGY).

Geriatric Use

The effect of age on induction dose requirements for propofol was assessed in an open-label study involving 211 unpremedicated patients with approximately 30 patients in each decade between the ages of 16 and 80. The average dose to induce anesthesia was calculated for patients up to 54 years of age and for patients 55 years of age or older. The average dose to induce anesthesia in patients up to 54 years of age was 1.99 mg/kg and in patients above 54 it was 1.66 mg/kg. Subsequent clinical studies have demonstrated lower dosing requirements for subjects greater than 60 years of age.

A lower induction dose and a slower maintenance rate of administration of DIPRIVAN should be used in elderly patients. In this group of patients, rapid (single or repeated) bolus administration should not be used in order to minimize undesirable cardiorespiratory depression including hypotension, apnea, airway obstruction, and/or oxygen desaturation. All dosing should be titrated according to patient condition and response (see DOSAGE AND ADMINISTRATION, Elderly, Debilitated or ASA-PS III or IV Patients and CLINICAL PHARMACOLOGY, Geriatrics).

ADVERSE REACTIONS:

To report SUSPECTED ADVERSE REACTIONS, contact Fresenius Kabi USA, LLC at 1-800-551-7176 or FDA at 1-800-FDA-1088 or www.fda.gov/medwatch.

General

Adverse event information is derived from controlled clinical trials and worldwide marketing experience. In the description below, rates of the more common events represent US/Canadian clinical study results. Less frequent events are also derived from publications and marketing experience in over 8 million patients; there are insufficient data to support an accurate estimate of their incidence rates. These studies were conducted using a variety of premedicants, varying lengths of surgical/diagnostic procedures, and various other anesthetic/sedative agents. Most adverse events were mild and transient.

Anesthesia and MAC Sedation in Adults

The following estimates of adverse events for DIPRIVAN include data from clinical trials in general anesthesia/MAC sedation (N=2,889 adult patients). The adverse events listed below as probably causally related are those events in which the actual incidence rate in patients treated with DIPRIVAN was greater than the comparator incidence rate in these trials. Therefore, incidence rates for anesthesia and MAC sedation in adults generally represent estimates of the percentage of clinical trial patients which appeared to have probable causal relationship.

The adverse experience profile from reports of 150 patients in the MAC sedation clinical trials is similar to the profile established with DIPRIVAN during anesthesia (see below). During MAC sedation clinical trials, significant respiratory events included cough, upper airway obstruction, apnea, hypoventilation, and dyspnea.

Anesthesia in Pediatric Patients

Generally the adverse experience profile from reports of 506 DIPRIVAN pediatric patients from 6 days through 16 years of age in the US/Canadian anesthesia clinical trials is similar to the profile established with DIPRIVAN during anesthesia in adults (see Pediatric percentages [Peds %] below). Although not reported as an adverse event in clinical trials, apnea is frequently observed in pediatric patients.

ICU Sedation in Adults

The following estimates of adverse events include data from clinical trials in ICU sedation (N=159 adult patients). Probably related incidence rates for ICU sedation were determined by individual case report form review. Probable causality was based upon an apparent dose response relationship and/or positive responses to rechallenge. In many instances the presence of concomitant disease and concomitant therapy made the causal relationship unknown. Therefore, incidence rates for ICU sedation generally represent estimates of the percentage of clinical trial patients which appeared to have a probable causal relationship.

Incidence greater than 1% - Probably Causally Related

 | Anesthesia/MAC Sedation | ICU Sedation
Cardiovascular: | Bradycardia | Bradycardia Decreased Cardiac Output Hypotension 26%
Cardiovascular: | Arrhythmia [Peds: 1.2%] | Bradycardia Decreased Cardiac Output Hypotension 26%
Cardiovascular: | Tachycardia Nodal [Peds: 1.6%] | Bradycardia Decreased Cardiac Output Hypotension 26%
Cardiovascular: | Hypotension* [Peds: 17%](see also CLINICAL PHARMACOLOGY) | Bradycardia Decreased Cardiac Output Hypotension 26%
Cardiovascular: | Hypertension [Peds: 8%] | Bradycardia Decreased Cardiac Output Hypotension 26%
Central Nervous System: | Movement* [Peds: 17%]
Injection Site: | Burning/Stinging or Pain, 17.6% [Peds:10%]
Metabolic/Nutritional: |  | Hyperlipemia*
Respiratory: | Apnea (see also CLINICAL PHARMACOLOGY) | Respiratory Acidosis During Weaning*
Skin and Appendages: | Rash [Peds: 5%] Pruritus [Peds: 2%]

Events without an * or % had an incidence of 1% to 3%

*Incidence of events 3% to 10%

Incidence less than 1% - Probably Causally Related

 | Anesthesia MAC Sedation | ICU Sedation
Body as a Whole: | Anaphylaxis/Anaphylactoid Reaction
 | Perinatal Disorder Tachycardia Bigeminy Bradycardia Premature Ventricular Contractions Hemorrhage ECG Abnormal Arrhythmia Atrial Fever Extremities Pain Anticholinergic Syndrome
Cardiovascular: | Premature Atrial Contractions Syncope
Central Nervous System: | Hypertonia/Dystonia, Paresthesia | Agitation
Digestive: | Hypersalivation Nausea
Hemic/Lymphatic: | Leukocytosis
Injection Site: | Phlebitis Pruritus
Metabolic: | Hypomagnesemia
Musculoskeletal: | Myalgia
Nervous: | Dizziness Agitation Chills Somnolence Delirium
Respiratory: | Wheezing Cough Laryngospasm Hypoxia | Decreased Lung Function
Skin and Appendages: | Flushing, Pruritus
Special Senses: | Amblyopia Vision Abnormal
Urogenital: | Cloudy Urine | Green Urine

Incidence less than 1% - Causal Relationship Unknown

 | Anesthesia/MAC Sedation | ICU Sedation
Body as a Whole: | Asthenia, Awareness, Chest Pain, Extremities Pain, Fever, Increased Drug Effect, Neck Rigidity/Stiffness, Trunk Pain | Fever, Sepsis, Trunk Pain, Whole Body Weakness
Cardiovascular: | Arrhythmia, Atrial Fibrillation, Atrioventricular Heart Block, Bigeminy, Bleeding, Bundle Branch Block, Cardiac Arrest, ECG Abnormal, Edema, Extrasystole, Heart Block, Hypertension, Myocardial Infarction, Myocardial Ischemia, Premature Ventricular Contractions, ST Segment Depression, Supraventricular Tachycardia, Tachycardia, Ventricular Fibrillation | Arrhythmia, Atrial Fibrillation, Bigeminy, Cardiac Arrest, Extrasystole, Right Heart Failure, Ventricular Tachycardia
Central Nervous System: | Abnormal Dreams, Agitation, Amorous Behavior, Anxiety, Bucking/Jerking/Thrashing, Chills/Shivering/Clonic/Myoclonic Movement, Combativeness, Confusion, Delirium, Depression, Dizziness, Emotional Lability, Euphoria, Fatigue, Hallucinations, Headache, Hypotonia, Hysteria, Insomnia, Moaning, Neuropathy, Opisthotonos, Rigidity, Seizures, Somnolence, Tremor, Twitching | Chills/Shivering, Intracranial Hypertension, Seizures, Somnolence, Thinking Abnormal
Digestive: | Cramping, Diarrhea, Dry Mouth, Enlarged Parotid, Nausea, Swallowing,Vomiting | Ileus, Liver Function Abnormal
Hematologic/Lymphatic: | Coagulation Disorder, Leukocytosis
Injection Site: | Hives/Itching, Phlebitis, Redness/Discoloration
Metabolic/Nutritional: | Hyperkalemia, Hyperlipemia | BUN Increased, Creatinine Increased, Dehydration, Hyperglycemia, Metabolic Acidosis, Osmolality Increased
Respiratory: | Bronchospasm, Burning in Throat, Cough, Dyspnea, Hiccough, Hyperventilation, Hypoventilation, Hypoxia, Laryngospasm, Pharyngitis, Sneezing, Tachypnea, Upper Airway Obstruction | Hypoxia
Skin and Appendages: | Conjunctival Hyperemia, Diaphoresis, Urticaria | Rash
Special Senses: | Diplopia, Ear Pain, Eye Pain, Nystagmus, Taste Perversion, Tinnitus
Urogenital: | Oliguria, Urine Retention | Kidney Failure

DRUG ABUSE AND DEPENDENCE:

There are reports of the abuse of propofol for recreational and other improper purposes, which have resulted in fatalities and other injuries. Instances of self-administration of DIPRIVAN by health care professionals have also been reported, which have resulted in fatalities and other injuries. Inventories of DIPRIVAN should be stored and managed to prevent the risk of diversion, including restriction of access and accounting procedures as appropriate to the clinical setting.

OVERDOSAGE:

If overdosage occurs, DIPRIVAN administration should be discontinued immediately. Overdosage is likely to cause cardiorespiratory depression. Respiratory depression should be treated by artificial ventilation with oxygen. Cardiovascular depression may require repositioning of the patient by raising the patient's legs, increasing the flow rate of intravenous fluids, and administering pressor agents and/or anticholinergic agents.

DOSAGE AND ADMINISTRATION:

Propofol blood concentrations at steady-state are generally proportional to infusion rates, especially in individual patients. Undesirable effects such as cardiorespiratory depression are likely to occur at higher blood concentrations which result from bolus dosing or rapid increases in the infusion rate. An adequate interval (3 minutes to 5 minutes) must be allowed between dose adjustments to allow for and assess the clinical effects.

Shake well before use. Do not use if there is evidence of excessive creaming or aggregation, if large droplets are visible, or if there are other forms of phase separation indicating that the stability of the product has been compromised. Slight creaming, which should disappear after shaking, may be visible upon prolonged standing.

When administering DIPRIVAN by infusion, syringe or volumetric pumps are recommended to provide controlled infusion rates. When infusing DIPRIVAN to patients undergoing magnetic resonance imaging, metered control devices may be utilized if mechanical pumps are impractical.

Changes in vital signs indicating a stress response to surgical stimulation or the emergence from anesthesia may be controlled by the administration of 25 mg (2.5 mL) to 50 mg (5 mL) incremental boluses and/or by increasing the infusion rate of DIPRIVAN.

For minor surgical procedures (e.g., body surface) nitrous oxide (60% to 70%) can be combined with a variable rate DIPRIVAN infusion to provide satisfactory anesthesia. With more stimulating surgical procedures (e.g., intra-abdominal), or if supplementation with nitrous oxide is not provided, administration rate(s) of DIPRIVAN and/or opioids should be increased in order to provide adequate anesthesia.

Infusion rates should always be titrated downward in the absence of clinical signs of light anesthesia until a mild response to surgical stimulation is obtained in order to avoid administration of DIPRIVAN at rates higher than are clinically necessary. Generally, rates of 50 mcg/kg/min to 100 mcg/kg/min in adults should be achieved during maintenance in order to optimize recovery times.

Other drugs that cause CNS depression (e.g., sedatives, anesthetics, and opioids) can increase CNS depression induced by propofol. Morphine premedication (0.15 mg/kg) with nitrous oxide 67% in oxygen has been shown to decrease the necessary propofol injection maintenance infusion rate and therapeutic blood concentrations when compared to non-narcotic (lorazepam) premedication.

Induction of General Anesthesia

Adult Patients

Most adult patients under 55 years of age and classified as ASA-PS I or II require 2 mg/kg to

2.5 mg/kg of DIPRIVAN for induction when unpremedicated or when premedicated with oral benzodiazepines or intramuscular opioids. For induction, DIPRIVAN should be titrated (approximately 40 mg every 10 seconds) against the response of the patient until the clinical signs show the onset of anesthesia. As with other general anesthetics, the amount of intravenous opioid and/or benzodiazepine premedication will influence the response of the patient to an induction dose of DIPRIVAN.

Elderly, Debilitated, or ASA-PS III or IV Patients

It is important to be familiar and experienced with the intravenous use of DIPRIVAN before treating elderly, debilitated, or ASA-PS III or IV patients. Due to the reduced clearance and higher blood concentrations, most of these patients require approximately 1 mg/kg to 1.5 mg/kg (approximately 20 mg every 10 seconds) of DIPRIVAN for induction of anesthesia according to their condition and responses. A rapid bolus should not be used, as this will increase the likelihood of undesirable cardiorespiratory depression including hypotension, apnea, airway obstruction, and/or oxygen desaturation (see DOSAGE AND ADMINISTRATION).

Pediatric Patients

Most patients aged 3 years through 16 years and classified ASA-PS I or II require 2.5 mg/kg to 3.5 mg/kg of DIPRIVAN for induction when unpremedicated or when lightly premedicated with oral benzodiazepines or intramuscular opioids. Within this dosage range, younger pediatric patients may require higher induction doses than older pediatric patients. As with other general anesthetics, the amount of intravenous opioid and/or benzodiazepine premedication will influence the response of the patient to an induction dose of DIPRIVAN. A lower dosage is recommended for pediatric patients classified as ASA-PS III or IV. Attention should be paid to minimize pain on injection when administering DIPRIVAN to pediatric patients. Boluses of DIPRIVAN may be administered via small veins if pretreated with lidocaine or via antecubital or larger veins (see PRECAUTIONS, General).

Neurosurgical Patients

Slower induction is recommended using boluses of 20 mg every 10 seconds. Slower boluses or infusions of DIPRIVAN for induction of anesthesia, titrated to clinical responses, will generally result in reduced induction dosage requirements (1 mg/kg to 2 mg/kg) (see PRECAUTIONS and DOSAGE AND ADMINISTRATION).

Cardiac Anesthesia

DIPRIVAN has been well-studied in patients with coronary artery disease, but experience in patients with hemodynamically significant valvular or congenital heart disease is limited. As with other general anesthetics and sedation drugs, DIPRIVAN in healthy patients causes a decrease in blood pressure that is secondary to decreases in preload (ventricular filling volume at the end of the diastole) and afterload (arterial resistance at the beginning of the systole). The magnitude of these changes is proportional to the blood and effect site concentrations achieved. These concentrations depend upon the dose and speed of the induction and maintenance infusion rates.

In addition, lower heart rates are observed during maintenance with DIPRIVAN, possibly due to reduction of the sympathetic activity and/or resetting of the baroreceptor reflexes. Therefore, anticholinergic agents should be administered when increases in vagal tone are anticipated.

As with other anesthetic agents, DIPRIVAN reduces myocardial oxygen consumption. Further studies are needed to confirm and delineate the extent of these effects on the myocardium and the coronary vascular system.

Morphine premedication (0.15 mg/kg) with nitrous oxide 67% in oxygen has been shown to decrease the necessary DIPRIVAN maintenance infusion rates and therapeutic blood concentrations when compared to non-narcotic (lorazepam) premedication. The rate of DIPRIVAN administration should be determined based on the patient's premedication and adjusted according to clinical responses.

A rapid bolus induction should be avoided. A slow rate of approximately 20 mg every 10 seconds until induction onset (0.5 mg/kg to 1.5 mg/kg) should be used. In order to assure adequate anesthesia, when DIPRIVAN is used as the primary agent, maintenance infusion rates should not be less than 100 mcg/kg/min and should be supplemented with analgesic levels of continuous opioid administration. When an opioid is used as the primary agent, DIPRIVAN maintenance rates should not be less than 50 mcg/kg/min, and care should be taken to ensure amnesia. Higher doses of DIPRIVAN will reduce the opioid requirements (see Table 4). When DIPRIVAN is used as the primary anesthetic, it should not be administered with the high-dose opioid technique as this may increase the likelihood of hypotension (see PRECAUTIONS, Cardiac Anesthesia).

Table 4. Cardiac Anesthesia Techniques

Primary Agent | Rate | Secondary Agent/Rate (Following Induction with Primary Agent)
DIPRIVAN |  | OPIOIDa/0.05 mcg/kg/min to 0.075 mcg/kg/min (no bolus)
Preinduction Anxiolysis | 25 mcg/kg/min
Induction | 0.5 mg/kg to 1.5 mg/kg over 60 sec
Maintenance (Titrated to Clinical Response) | 100 mcg/kg/min to 150 mcg/kg/min
OPIOIDb |  | DIPRIVAN /50 mcg/kg/min to 100 mcg/kg/min (no bolus)
Induction | 25 mcg/kg to 50 mcg/kg
Maintenance | 0.2 mcg/kg/min to 0.3 mcg/kg/min

aOPIOID is defined in terms of fentanyl equivalents, i.e.,

1 mcg of fentanyl = 5 mcg of alfentanil (for bolus)

= 10 mcg of alfentanil (for maintenance)

or

= 0.1 mcg of sufentanil

bCare should be taken to ensure amnesia.

Maintenance of General Anesthesia

DIPRIVAN has been used with a variety of agents commonly used in anesthesia such as atropine, scopolamine, glycopyrrolate, diazepam, depolarizing and nondepolarizing muscle relaxants, and opioid analgesics, as well as with inhalational and regional anesthetic agents.

In the elderly, debilitated, or ASA-PS III or IV patients, rapid bolus doses should not be used, as this will increase cardiorespiratory effects including hypotension, apnea, airway obstruction, and oxygen desaturation.

Adult Patients

In adults, anesthesia can be maintained by administering DIPRIVAN by infusion or intermittent IV bolus injection. The patient's clinical response will determine the infusion rate or the amount and frequency of incremental injections.

Continuous Infusion

DIPRIVAN 100 mcg/kg/min to 200 mcg/kg/min administered in a variable rate infusion with 60% to 70% nitrous oxide and oxygen provides anesthesia for patients undergoing general surgery. Maintenance by infusion of DIPRIVAN should immediately follow the induction dose in order to provide satisfactory or continuous anesthesia during the induction phase. During this initial period following the induction dose, higher rates of infusion are generally required (150 mcg/kg/min to 200 mcg/kg/min) for the first 10 minutes to 15 minutes. Infusion rates should subsequently be decreased 30% to 50% during the first half-hour of maintenance. Generally, rates of 50 mcg/kg/min to 100 mcg/kg/min in adults should be achieved during maintenance in order to optimize recovery times.

Other drugs that cause CNS depression (e.g., sedatives, anesthetics, and opioids) can increase the CNS depression induced by propofol.

Intermittent Bolus

Increments of DIPRIVAN 25 mg (2.5 mL) to 50 mg (5 mL) may be administered with nitrous oxide in adult patients undergoing general surgery. The incremental boluses should be administered when changes in vital signs indicate a response to surgical stimulation or light anesthesia.

Pediatric Patients

DIPRIVAN administered as a variable rate infusion supplemented with nitrous oxide 60% to 70% provides satisfactory anesthesia for most children 2 months of age or older, ASA-PS I or II, undergoing general anesthesia.

In general, for the pediatric population, maintenance by infusion of DIPRIVAN at a rate of 200 mcg/kg/min to 300 mcg/kg/min should immediately follow the induction dose. Following the first half-hour of maintenance, infusion rates of 125 mcg/kg/min to 150 mcg/kg/min are typically needed. DIPRIVAN should be titrated to achieve the desired clinical effect. Younger pediatric patients may require higher maintenance infusion rates than older pediatric patients. (See Table 2 Clinical Trials.)

Monitored Anesthesia Care (MAC) Sedation

Adult Patients

When DIPRIVAN is administered for MAC sedation, rates of administration should be individualized and titrated to clinical response. In most patients, the rates of DIPRIVAN administration will be in the range of 25 mcg/kg/min to 75 mcg/kg/min.

During initiation of MAC sedation, slow infusion or slow injection techniques are preferable over rapid bolus administration. During maintenance of MAC sedation, a variable rate infusion is preferable over intermittent bolus dose administration. In the elderly, debilitated, or ASA-PS III or IV patients, rapid (single or repeated) bolus dose administration should not be used for MAC sedation (see WARNINGS). A rapid bolus injection can result in undesirable cardiorespiratory depression including hypotension, apnea, airway obstruction, and oxygen desaturation.

Initiation of MAC Sedation

For initiation of MAC sedation, either an infusion or a slow injection method may be utilized while closely monitoring cardiorespiratory function. With the infusion method, sedation may be initiated by infusing DIPRIVAN at 100 mcg/kg/min to 150 mcg/kg/min (6 mg/kg/h to 9 mg/kg/h) for a period of 3 minutes to 5 minutes and titrating to the desired clinical effect while closely monitoring respiratory function. With the slow injection method for initiation, patients will require approximately 0.5 mg/kg administered over 3 minutes to 5 minutes and titrated to clinical responses. When DIPRIVAN is administered slowly over 3 minutes to 5 minutes, most patients will be adequately sedated, and the peak drug effect can be achieved while minimizing undesirable cardiorespiratory effects occurring at high plasma levels.

In the elderly, debilitated, or ASA-PS III or IV patients, rapid (single or repeated) bolus dose administration should not be used for MAC sedation (see WARNINGS). The rate of administration should be over 3 minutes to 5 minutes and the dosage of DIPRIVAN should be reduced to approximately 80% of the usual adult dosage in these patients according to their condition, responses, and changes in vital signs (see DOSAGE AND ADMINISTRATION).

Maintenance of MAC Sedation

For maintenance of sedation, a variable rate infusion method is preferable over an intermittent bolus dose method. With the variable rate infusion method, patients will generally require maintenance rates of 25 mcg/kg/min to 75 mcg/kg/min (1.5 mg/kg/h to 4.5 mg/kg/h) during the first 10 minutes to 15 minutes of sedation maintenance. Infusion rates should subsequently be decreased over time to 25 mcg/kg/min to 50 mcg/kg/min and adjusted to clinical responses. In titrating to clinical effect, allow approximately 2 minutes for onset of peak drug effect.

Infusion rates should always be titrated downward in the absence of clinical signs of light sedation until mild responses to stimulation are obtained in order to avoid sedative administration of DIPRIVAN at rates higher than are clinically necessary.

If the intermittent bolus dose method is used, increments of DIPRIVAN 10 mg (1 mL) or 20 mg (2 mL) can be administered and titrated to desired clinical effect. With the intermittent bolus method of sedation maintenance, there is increased potential for respiratory depression, transient increases in sedation depth, and prolongation of recovery.

In the elderly, debilitated, or ASA-PS III or IV patients, rapid (single or repeated) bolus dose administration should not be used for MAC sedation (see WARNINGS). The rate of administration and the dosage of DIPRIVAN should be reduced to approximately 80% of the usual adult dosage in these patients according to their condition, responses, and changes in vital signs (see DOSAGE AND ADMINISTRATION).

DIPRIVAN can be administered as the sole agent for maintenance of MAC sedation during surgical/diagnostic procedures. When DIPRIVAN sedation is supplemented with opioid and/or benzodiazepine medications, these agents increase the sedative and respiratory effects of DIPRIVAN and may also result in a slower recovery profile (see PRECAUTIONS, Drug Interactions).

ICU Sedation

(See WARNINGS and DOSAGE AND ADMINISTRATION, Handling Procedures.)

Abrupt discontinuation of DIPRIVAN prior to weaning or for daily evaluation of sedation levels should be avoided. This may result in rapid awakening with associated anxiety, agitation, and resistance to mechanical ventilation. Infusions of DIPRIVAN should be adjusted to assure a minimal level of sedation is maintained throughout the weaning process and when assessing the level of sedation (see PRECAUTIONS).

Adult Patients

For intubated, mechanically ventilated adult patients, Intensive Care Unit (ICU) sedation should be initiated slowly with a continuous infusion in order to titrate to desired clinical effect and minimize hypotension (see DOSAGE AND ADMINISTRATION).

Most adult ICU patients recovering from the effects of general anesthesia or deep sedation will require maintenance rates of 5 mcg/kg/min to 50 mcg/kg/min (0.3 mg/kg/h to 3 mg/kg/h) individualized and titrated to clinical response (see DOSAGE AND ADMINISTRATION). With medical ICU patients or patients who have recovered from the effects of general anesthesia or deep sedation, the rate of administration of 50 mcg/kg/min or higher may be required to achieve adequate sedation. These higher rates of administration may increase the likelihood of patients developing hypotension. Administration should not exceed 4 mg/kg/hour unless the benefits outweigh the risks (see WARNINGS).

Dosage and rate of administration should be individualized and titrated to the desired effect, according to clinically relevant factors including the patient’s underlying medical problems, preinduction and concomitant medications, age, ASA-PS classification, and level of debilitation of the patient. The elderly, debilitated, and ASA-PS III or IV patients may have exaggerated hemodynamic and respiratory responses to rapid bolus doses (see WARNINGS).

DIPRIVAN should be individualized according to the patient's condition and response, blood lipid profile, and vital signs (see PRECAUTIONS, Intensive Care Unit Sedation). For intubated, mechanically ventilated adult patients, Intensive Care Unit (ICU) sedation should be initiated slowly with a continuous infusion in order to titrate to desired clinical effect and minimize hypotension. When indicated, initiation of sedation should begin at 5 mcg/kg/min (0.3 mg/kg/h). The infusion rate should be increased by increments of 5 mcg/kg/min to 10 mcg/kg/min (0.3 mg/kg/h to 0.6 mg/kg/h) until the desired level of sedation is achieved. A minimum period of 5 minutes between adjustments should be allowed for onset of peak drug effect. Most adult patients require maintenance rates of 5 mcg/kg/min to 50 mcg/kg/min (0.3 mg/kg/h to 3 mg/kg/h) or higher. Administration should not exceed 4 mg/kg/hour unless the benefits outweigh the risks (see WARNINGS). Dosages of DIPRIVAN should be reduced in patients who have received large dosages of narcotics. The DIPRIVAN dosage requirement may also be reduced by adequate management of pain with analgesic agents. As with other sedative medications, there is interpatient variability in dosage requirements, and these requirements may change with time (see SUMMARY OF DOSAGE GUIDELINES). Evaluation of level of sedation and assessment of CNS function should be carried out daily throughout maintenance to determine the minimum dose of DIPRIVAN required for sedation (see Clinical Trials, Intensive Care Unit (ICU) Sedation). Bolus administration of 10 mg or 20 mg should only be used to rapidly increase depth of sedation in patients where hypotension is not likely to occur. Patients with compromised myocardial function, intravascular volume depletion, or abnormally low vascular tone (e.g., sepsis) may be more susceptible to hypotension (see PRECAUTIONS).
SUMMARY OF DOSAGE GUIDELINES:

Dosages and rates of administration in the following table should be individualized and titrated to clinical response. Safety and dosing requirements for induction of anesthesia in pediatric patients have only been established for children 3 years of age or older. Safety and dosing requirements for the maintenance of anesthesia have only been established for children 2 months of age and older.

For complete dosage information, see DOSAGE AND ADMINISTRATION.

INDICATION | DOSAGE AND ADMINISTRATION
Induction of General Anesthesia: | Healthy Adults Less Than 55 Years of Age: 40 mg every 10 seconds until induction onset (2 mg/kg to 2.5 mg/kg). Elderly, Debilitated, or ASA-PS III or IV Patients: 20 mg every 10 seconds until induction onset (1 mg/kg to 1.5 mg/kg). Cardiac Anesthesia: 20 mg every 10 seconds until induction onset (0.5 mg/kg to 1.5 mg/kg). Neurosurgical Patients: 20 mg every 10 seconds until induction onset (1 mg/kg to 2 mg/kg). Pediatric Patients - healthy, from 3 years to 16 years of age: 2.5 mg/kg to 3.5 mg/kg administered over 20 seconds to 30 seconds. (see PRECAUTIONS, Pediatric Use and CLINICAL PHARMACOLOGY, Pediatrics).
Maintenance of General Anesthesia: | Infusion Healthy Adults Less Than 55 Years of Age: 100 mcg/kg/min to 200 mcg/kg/min (6 mg/kg/h to 12 mg/kg/h). Elderly, Debilitated, ASA-PS III or IV Patients: 50 mcg/kg/min to 100 mcg/kg/min (3 mg/kg/h to 6 mg/kg/h). Cardiac Anesthesia: Most patients require: Primary DIPRIVAN with Secondary Opioid – 100 mcg/kg/min to 150 mcg/kg/min. Low-Dose DIPRIVAN with Primary Opioid – 50 mcg/kg/min to 100 mcg/kg/min. (see DOSAGE AND ADMINISTRATION, Table 4). Neurosurgical Patients: 100 mcg/kg/min to 200 mcg/kg/min (6 mg/kg/h to 12 mg/kg/h). Pediatric Patients - healthy, from 2 months of age to 16 years of age: 125 mcg/kg/min to 300 mcg/kg/min (7.5 mg/kg/h to 18 mg/kg/h). Following the first half hour of maintenance, if clinical signs of light anesthesia are not present, the infusion rate should be decreased. (see PRECAUTIONS, Pediatric Use and CLINICAL PHARMACOLOGY, Pediatrics).
Maintenance of General Anesthesia: | Intermittent Bolus Healthy Adults Less Than 55 Years of Age: Increments of 20 mg to 50 mg as needed.
Initiation of MAC Sedation: | Healthy Adults Less Than 55 Years of Age: Slow infusion or slow injection techniques are recommended to avoid apnea or hypotension. Most patients require an infusion of 100 mcg/kg/min to 150 mcg/kg/min (6 mg/kg/h to 9 mg/kg/h) for 3 minutes to 5 minutes or a slow injection of 0.5 mg/kg over 3 minutes to 5 minutes followed immediately by a maintenance infusion. Elderly, Debilitated, Neurosurgical, or ASA-PS III or IV Patients: Most patients require dosages similar to healthy adults. Rapid boluses are to be avoided (see WARNINGS).
Maintenance of MAC Sedation: | Healthy Adults Less Than 55 Years of Age: A variable rate infusion technique is preferable over an intermittent bolus technique. Most patients require an infusion of 25 mcg/kg/min to 75 mcg/kg/min (1.5 mg/kg/h to 4.5 mg/kg/h) or incremental bolus doses of 10 mg or 20 mg. In Elderly, Debilitated, Neurosurgical, or ASA-PS III or IV Patients: Most patients require 80% of the usual adult dose. A rapid (single or repeated) bolus dose should not be used (see WARNINGS).
Initiation and Maintenance of ICU Sedation in Intubated, Mechanically Ventilated
 | Adult Patients - Because of the residual effects of previous anesthetic or sedative agents, in most patients the initial infusion should be 5 mcg/kg/min (0.3 mg/kg/h) for at least 5 minutes. Subsequent increments of 5 mcg/kg/min to 10 mcg/kg/min (0.3 mg/kg/h to 0.6 mg/kg/h) over 5 minutes to 10 minutes may be used until desired clinical effect is achieved. Maintenance rates of 5 mcg/kg/min to 50 mcg/kg/min (0.3 mg/kg/h to 3 mg/kg/h) or higher may be required. Administration should not exceed 4 mg/kg/hour unless the benefits outweigh the risks (see WARNINGS). Evaluation of clinical effect and assessment of CNS function should be carried out daily throughout maintenance to determine the minimum dose of DIPRIVAN required for sedation. The tubing and any unused DIPRIVAN drug product should be discarded after 12 hours because DIPRIVAN contains no preservatives and is capable of supporting growth of microorganisms (see WARNINGS and DOSAGE AND ADMINISTRATION).

Administration with Lidocaine

If lidocaine is to be administered to minimize pain on injection of DIPRIVAN, it is recommended that it be administered prior to DIPRIVAN administration or that it be added to DIPRIVAN immediately before administration and in quantities not exceeding 20 mg lidocaine/200 mg DIPRIVAN.

Compatibility and Stability

DIPRIVAN should not be mixed with other therapeutic agents prior to administration.

Dilution Prior to Administration

DIPRIVAN is provided as a ready-to-use formulation. However, should dilution be necessary, it should only be diluted with 5% Dextrose Injection, USP, and it should not be diluted to a concentration less than 2 mg/mL because it is an emulsion. In diluted form it has been shown to be more stable when in contact with glass than with plastic (95% potency after 2 hours of running infusion in plastic).

Administration with Other Fluids

Compatibility of DIPRIVAN with the coadministration of blood/serum/plasma has not been established (see WARNINGS). When administered using a y-type infusion set, DIPRIVAN has been shown to be compatible with the following intravenous fluids.

- 5% Dextrose Injection, USP

- Lactated Ringers Injection, USP

- Lactated Ringers and 5% Dextrose Injection

- 5% Dextrose and 0.45% Sodium Chloride Injection, USP

- 5% Dextrose and 0.2% Sodium Chloride Injection, USP

Handling Procedures

General

Parenteral drug products should be inspected visually for particulate matter and discoloration prior to administration whenever solution and container permit.

Clinical experience with the use of in-line filters and DIPRIVAN during anesthesia or ICU/MAC sedation is limited. DIPRIVAN should only be administered through a filter with a pore size of 5 micron or greater unless it has been demonstrated that the filter does not restrict the flow of DIPRIVAN and/or cause the breakdown of the emulsion. Filters should be used with caution and where clinically appropriate. Continuous monitoring is necessary due to the potential for restricted flow and/or breakdown of the emulsion.

Do not use if there is evidence of separation of the phases of the emulsion.

Rare cases of self-administration of DIPRIVAN by health care professionals have been reported, including some fatalities (see DRUG ABUSE AND DEPENDENCE).

Strict aseptic technique must always be maintained during handling. DIPRIVAN is a single access parenteral product (single patient infusion vial) which contains 0.005% disodium edetate to inhibit the rate of growth of microorganisms, up to 12 hours, in the event of accidental extrinsic contamination. However, DIPRIVAN can still support the growth of microorganisms as it is not an antimicrobially preserved product under USP standards. Do not use if contamination is suspected. Discard unused drug product as directed within the required time limits. There have been reports in which failure to use aseptic technique when handling DIPRIVAN was associated with microbial contamination of the product and with fever, infection/sepsis, other life-threatening illness, and/or death.

There have been reports, in the literature and other public sources, of the transmission of bloodborne pathogens (such as Hepatitis B, Hepatitis C, and HIV) from unsafe injection practices, and use of propofol vials intended for single use on multiple persons. DIPRIVAN vials are never to be accessed more than once or used on more than one person.

Diprivan, with EDTA inhibits microbial growth for up to 12 hours, as demonstrated by test data for representative USP microorganisms.

Guidelines for Aseptic Technique for General Anesthesia/MAC Sedation

DIPRIVAN must be prepared for use just prior to initiation of each individual anesthetic/sedative procedure. The vial rubber stopper should be disinfected using 70% isopropyl alcohol. DIPRIVAN should be drawn into a sterile syringe immediately after a vial is opened. When withdrawing DIPRIVAN from vials, a sterile vent spike should be used. The syringe should be labeled with appropriate information including the date and time the vial was opened. Administration should commence promptly and be completed within 12 hours after the vial has been opened.

DIPRIVAN must be prepared for single-patient use only. Any unused DIPRIVAN drug product, reservoirs, dedicated administration tubing and/or solutions containing DIPRIVAN must be discarded at the end of the anesthetic procedure or at 12 hours, whichever occurs sooner. The IV line should be flushed every 12 hours and at the end of the anesthetic procedure to remove residual DIPRIVAN.

Guidelines for Aseptic Technique for ICU Sedation

DIPRIVAN must be prepared for single-patient use only. Strict aseptic techniques must be followed. The vial rubber stopper should be disinfected using 70% isopropyl alcohol. A sterile vent spike and sterile tubing must be used for administration of DIPRIVAN. As with other lipid emulsions, the number of IV line manipulations should be minimized. Administration should commence promptly and must be completed within 12 hours after the vial has been spiked. The tubing and any unused DIPRIVAN drug product must be discarded after 12 hours.

If DIPRIVAN is transferred to a syringe prior to administration, it should be drawn into a sterile syringe immediately after a vial is opened. When withdrawing DIPRIVAN from a vial, a sterile vent spike should be used. The syringe should be labeled with appropriate information including the date and time the vial was opened. Administration should commence promptly and be completed within 12 hours after the vial has been opened. DIPRIVAN should be discarded and administration lines changed after 12 hours.

HOW SUPPLIED:

DIPRIVAN (propofol) Injectable Emulsion, USP Vials

Product Code | Each | Unit of Sale | Strength
RF260929 | NDC 65219-800-01 20 mL ready-to-use single-dose vial for single patient use only. | NDC 65219-800-10 Packages of ten. This product contains an RFID. | 200 mg per 20 mL (10 mg per mL)
260929 | NDC 63323-269-22 20 mL ready-to-use single-dose vial for single patient use only. | NDC 63323-269-29 Packages of ten. | 200 mg per 20 mL (10 mg per mL)
260950 | NDC 63323-269-30 50 mL ready-to-use single-dose vial for single patient use only. | NDC 63323-269-50 Packages of twenty. | 500 mg per 50 mL (10 mg per mL)
260965 | NDC 63323-269-35 100 mL ready-to-use single-dose vial for single patient use only. | NDC 63323-269-65 Packages of ten. | 1,000 mg per 100 mL (10 mg per mL)

Propofol undergoes oxidative degradation, in the presence of oxygen, and is therefore packaged under nitrogen to eliminate this degradation path.

Store between 4° to 25°C (40° to 77°F). Do not freeze. Shake well before use.

All trademarks are the property of Fresenius Kabi USA, LLC.

ANIMAL TOXICOLOGY AND/OR PHARMACOLOGY

Published studies in animals demonstrate that the use of anesthetic agents during the period of rapid brain growth or synaptogenesis results in widespread neuronal and oligodendrocyte cell loss in the developing brain and alterations in synaptic morphology and neurogenesis. Based on comparisons across species, the window of vulnerability to these changes is believed to correlate with exposures in the third trimester through the first several months of life, but may extend out to approximately 3 years of age in humans.

In primates, exposure to 3 hours of an anesthetic regimen that produced a light surgical plane of anesthesia did not increase neuronal cell loss, however, treatment regimens of 5 hours or longer increased neuronal cell loss. Data in rodents and in primates suggest that the neuronal and oligodendrocyte cell losses are associated with subtle but prolonged cognitive deficits in learning and memory. The clinical significance of these nonclinical findings is not known, and healthcare providers should balance the benefits of appropriate anesthesia in neonates and young children who require procedures against the potential risks suggested by the nonclinical data (see WARNINGS, Pediatric Neurotoxicity, PRECAUTIONS; Pregnancy, Pediatric Use).

Manufactured for:
Lake Zurich, IL 60047
Made in Sweden

www.fresenius-kabi.com/us
451243F
Revised: September 2022

PACKAGE LABEL

PACKAGE LABEL - PRINCIPAL DISPLAY - Diprivan® 20 mL Vial Label

DIPRIVAN® (Propofol) INJECTABLE EMULSION, USP

200 mg per 20 mL (10 mg per mL)

FOR INTRAVENOUS ADMINISTRATION

20 mL Single-Dose Vial

SHAKE WELL BEFORE USING

PACKAGE LABEL

PACKAGE LABEL - PRINCIPAL DISPLAY - Diprivan® 20 mL Vial Carton Panel

NDC 65219-800-10 RF 260929

DIPRIVAN® (Propofol) INJECTABLE EMULSION, USP

200 mg per 20 mL (10 mg per mL)

FOR INTRAVENOUS ADMINISTRATION
SHAKE WELL BEFORE USING

Ten 20 mL vials

Single-Dose Vials